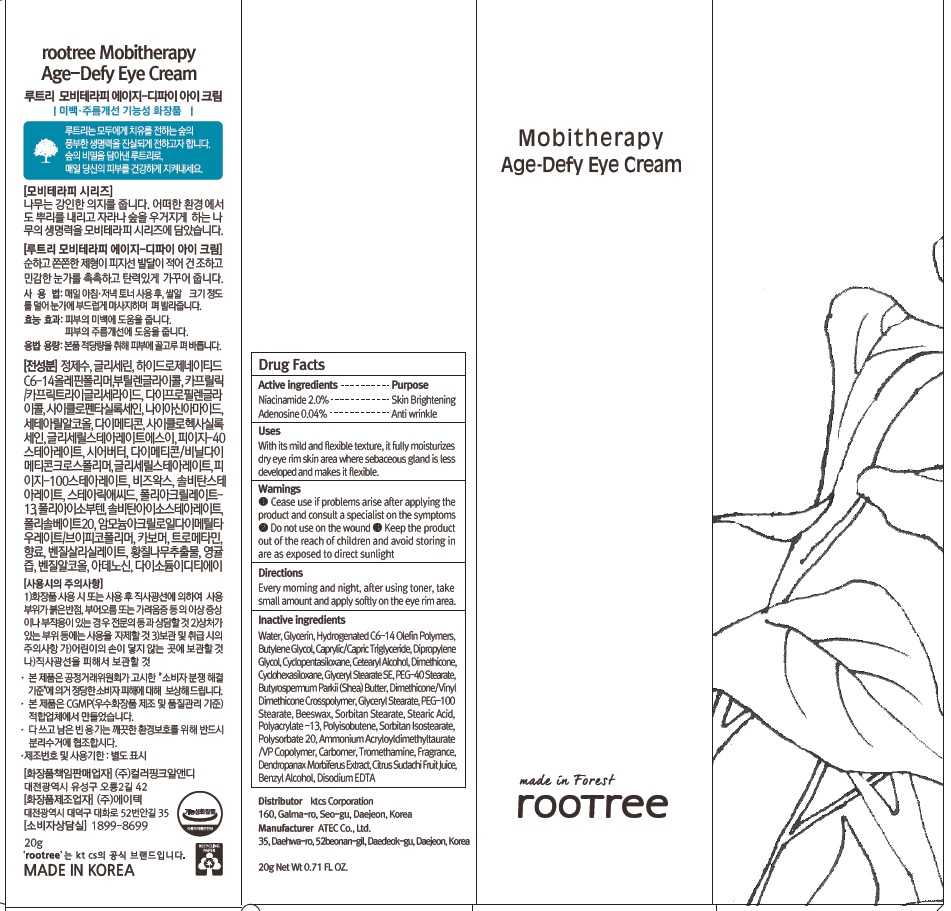 DRUG LABEL: rootree Mobitherapy Age Defy Eye
NDC: 72441-060 | Form: CREAM
Manufacturer: KTCS Corporation
Category: otc | Type: HUMAN OTC DRUG LABEL
Date: 20201231

ACTIVE INGREDIENTS: Niacinamide 0.4 g/20 g; Adenosine 0.008 g/20 g
INACTIVE INGREDIENTS: Water; Glycerin

ACTIVE INGREDIENTS

Niacinamide 2.0%, Adenosine 0.04%

INACTIVE INGREDIENTS

Water, Glycerin, Hydrogenated C6-14 Olefin Polymers, Butylene Glycol, Caprylic/Capric Triglyceride, Dipropylene Glycol, Cyclopentasiloxane, Cetearyl Alcohol, Dimethicone, Cyclohexasiloxane, Glyceryl Stearate SE, PEG-40 Stearate, Butyrospermum Parkii (Shea) Butter, Dimethicone/Vinyl Dimethicone Crosspolymer, Glyceryl Stearate, PEG-100 Stearate, Beeswax, Sorbitan Stearate, Stearic Acid, Polyacrylate-13, Polyisobutene, Sorbitan Isostearate, Polysorbate 20, Ammonium Acryloyldimethyltaurate/VP Copolymer, Carbomer, Tromethamine, Fragrance, Dendropanax Morbiferus Extract, Citrus Sudachi Fruit Juice, Benzyl Alcohol, Disodium EDTA

PURPOSE

Skin Brightening, Anti wrinkle

WARNINGS

- Cease use if problems arise after applying the product and consult a specialist on the symptoms.

- Do not use on the wound.
- Keep the product out of the reach of children and avoid storing in are as exposed to direct sunlight.

KEEP OUT OF REACH OF CHILDREN

Keep the product out of the reach of children

Uses

With its mild and flexible texture, it fully moisturizes dry eye rim skin area where sebaceous gland is less developed and makes it flexible.

Directions

Every morning and night, after using toner, take small amount size and apply softly on the eye rim area.